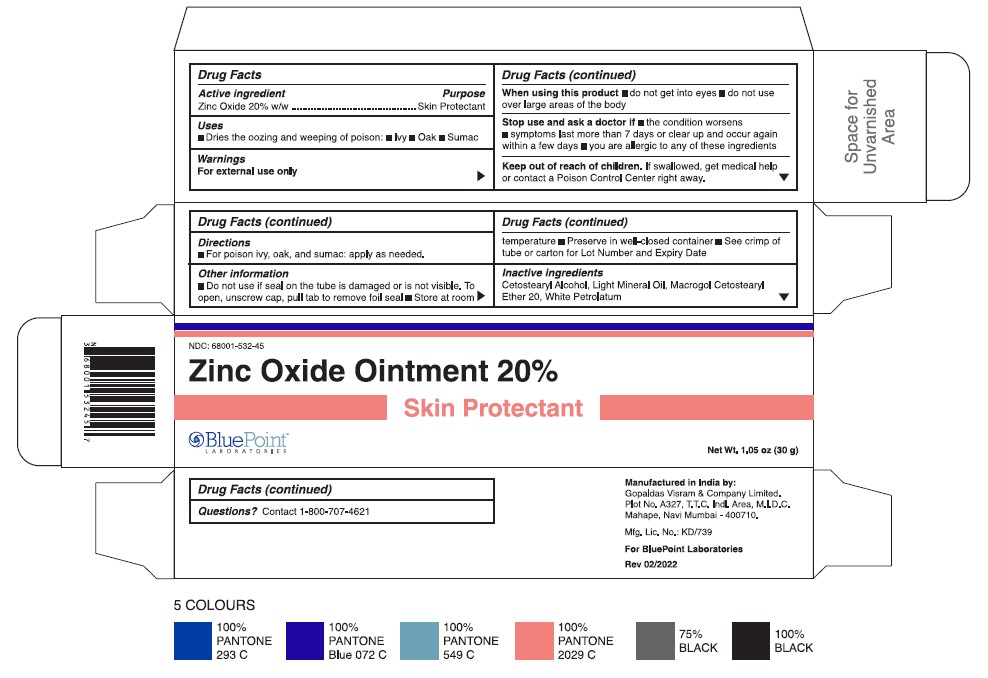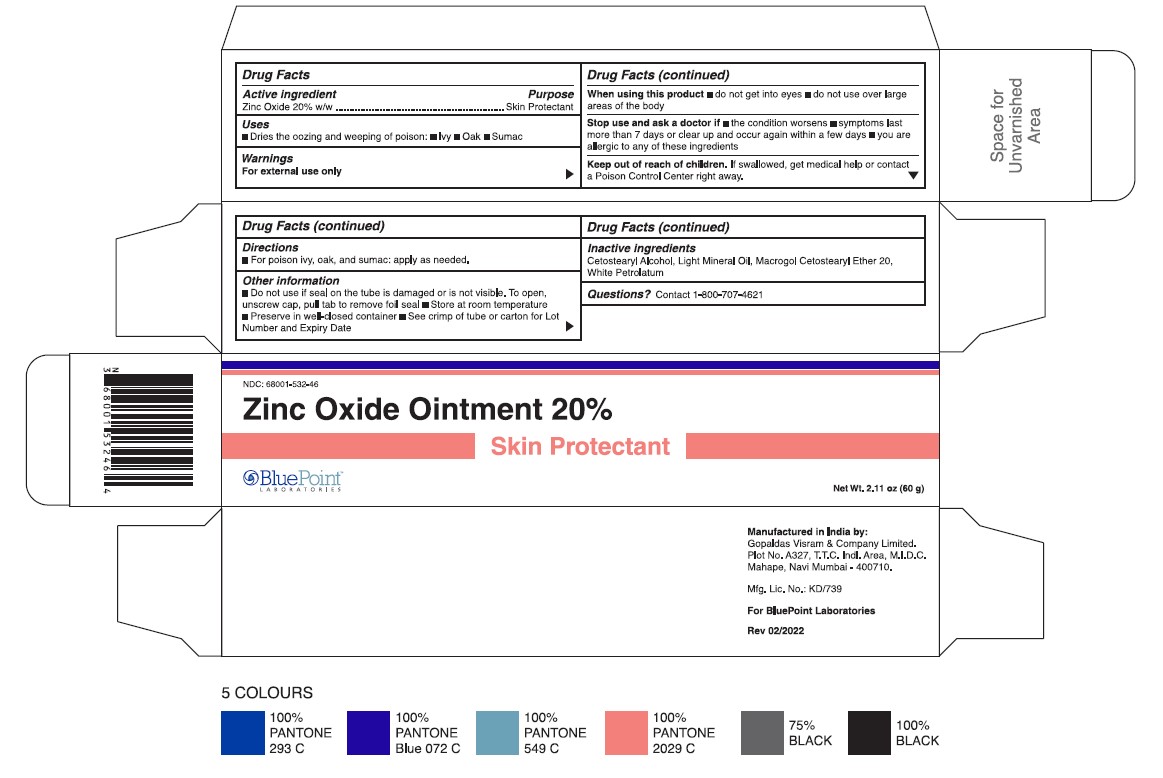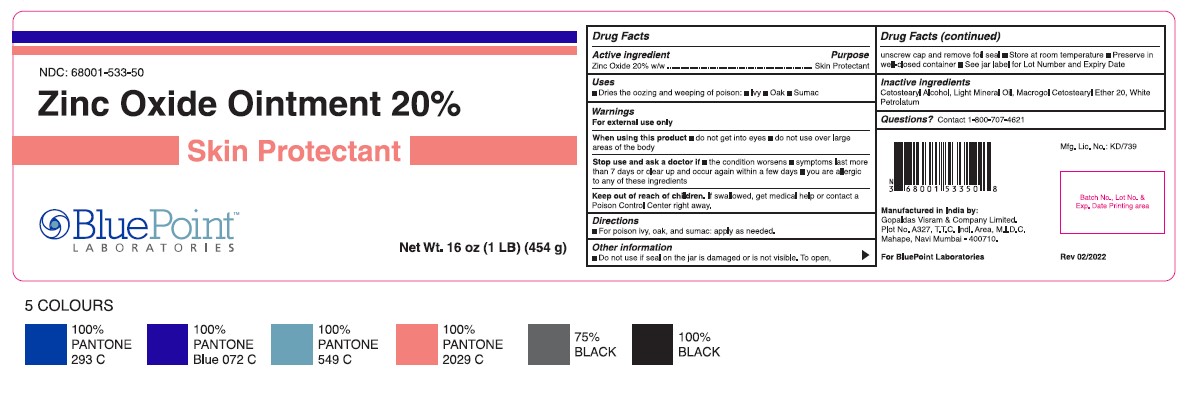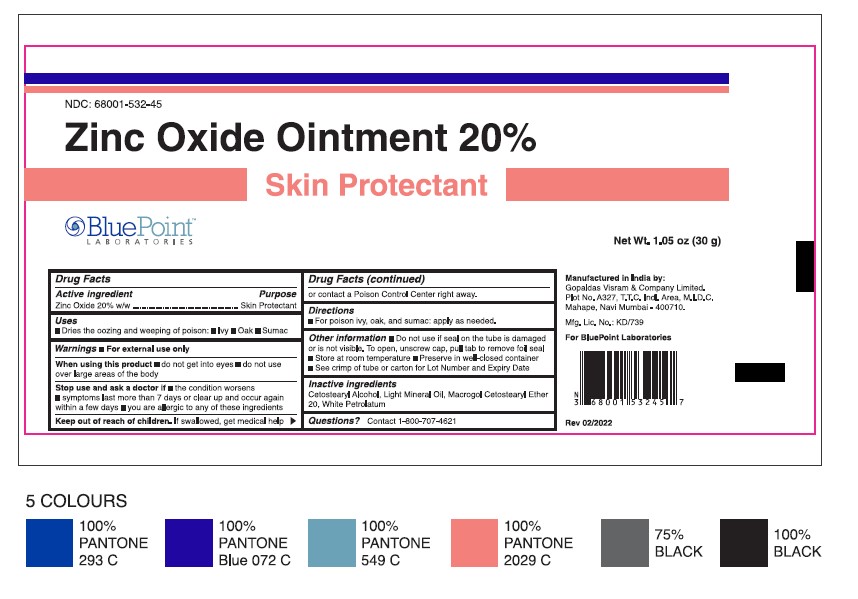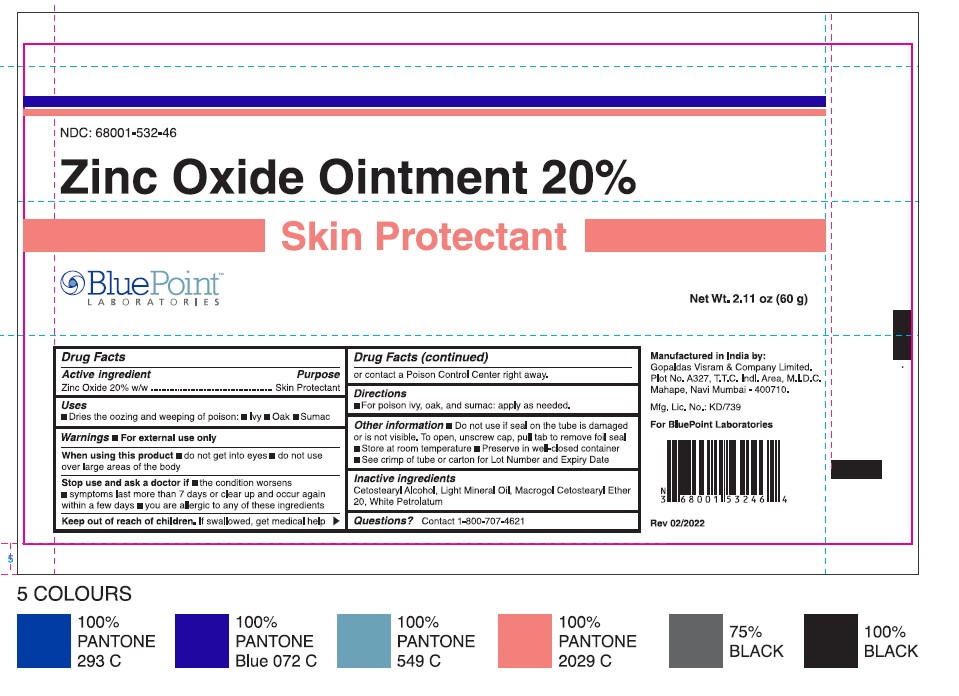 DRUG LABEL: Zinc Oxide
NDC: 68001-532 | Form: OINTMENT
Manufacturer: BluePoint Laboratories
Category: otc | Type: HUMAN OTC DRUG LABEL
Date: 20231117

ACTIVE INGREDIENTS: ZINC OXIDE 20 g/100 g
INACTIVE INGREDIENTS: LIGHT MINERAL OIL; CETOSTEARYL ALCOHOL; POLYOXYL 20 CETOSTEARYL ETHER; WHITE PETROLATUM

Zinc Oxide Ointment 20%

Active Ingredient

Zinc Oxide 20% w/w

Purpose

Skin Protectant

Uses

• Dries the oozing and weeping of poison: • Ivy • Oak • Sumac

Warnings

For External Use Only

When using this product

• Do not get into eyes

• Do not use over large areas of the body

Stop use and ask a doctor if

• The condition worsens

• Symptoms last more than 7 days or clear up and occur again within a few days

• You are allergic to any of these ingredients

Keep out of reach of children

If swallowed, get medical help or contact a Poison Control Center right away.

Directions

For poison ivy, oak, and sumac: apply as needed.

Other Information

- Do not use if seal on the tube is damaged or is not visible. To open, unscrew cap, pull tab to remove foil seal.
- Store at room temperature.
  - Preserve in well-closed container.
  - See crimp of tube or carton for Lot number and Expiry Date.

Inactive Ingredients

Cetostearyl Alcohol, Light Mineral Oil, Macrogol Cetostearyl Ether 20, White Petrolatum.

Questions?

Contact 1-800-707-4621

Gopaldas Visram & Company Limited.

Plot No. A327, T.T.C. Indl. Area, M.I.D.C.

Mahape, Navi Mumbai- 400710.

For BluePoint Laboratories